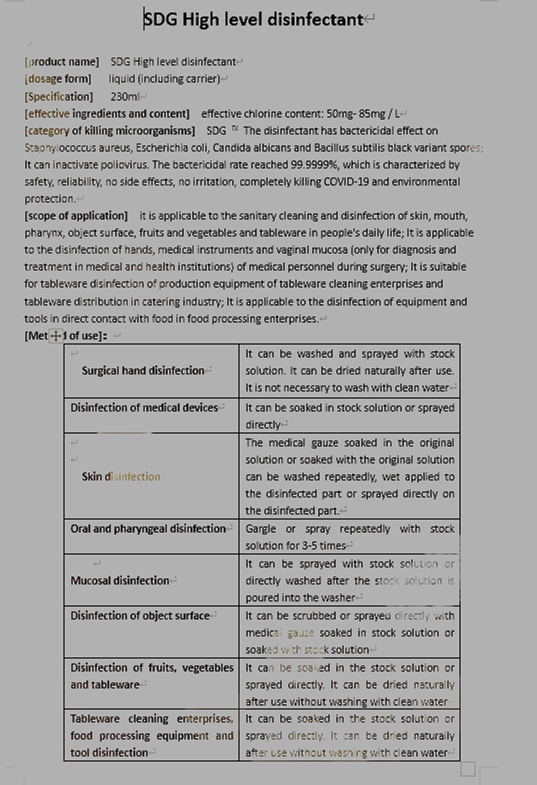 DRUG LABEL: SDG high level disinfectant
NDC: 82352-001 | Form: LIQUID
Manufacturer: Defeng Xingyuan (Jiangsu) Biotechnology Co., Ltd.
Category: otc | Type: HUMAN OTC DRUG LABEL
Date: 20211026

ACTIVE INGREDIENTS: SODIUM CHLORIDE 5 g/100 mL
INACTIVE INGREDIENTS: WATER

Method of use

Surgical hand disinfection:It can be washed and sprayed with stock solution. It can be dried naturally after use. It is not necessary to wash with clean water

Disinfection of medical devices:It can be soaked in stock solution or sprayed directly

Skin disinfection:The medical gauze soaked in the original solution or soaked with the original solution can be washed repeatedly, wet applied to the disinfected part or sprayed directly on the disinfected part.

Oral and pharyngeal disinfection:Gargle or spray repeatedly with stock solution for 3-5 times

Mucosal disinfection:It can be sprayed with stock solution or directly washed after the stock solution is poured into the washer

Disinfection of object surface:It can be scrubbed or sprayed directly with medical gauze soaked in stock solution or soaked with stock solution

Disinfection of fruits, vegetables and tableware:It can be soaked in the stock solution or sprayed directly. It can be dried naturally after use without washing with clean water

Tableware cleaning enterprises, food processing equipment and tool disinfection:It can be soaked in the stock solution or sprayed directly. It can be dried naturally after use without washing with clean water

INACTIVE INGREDIENT

WATER

scope of application

it is applicable to the sanitary cleaning and disinfection of skin, mouth, pharynx, object surface, fruits and vegetables and tableware in people's daily life; It is applicable to the disinfection of hands, medical instruments and vaginal mucosa (only for diagnosis and treatment in medical and health institutions) of medical personnel during surgery; It is suitable for tableware disinfection of production equipment of tableware cleaning enterprises and tableware distribution in catering industry; It is applicable to the disinfection of equipment and tools in direct contact with food in food processing enterprises.

ACTIVE INGREDIENT

Sodium chloride

keep out of reach of children

category of killing microorganisms

SDG ™ The disinfectant has bactericidal effect on Staphylococcus aureus, Escherichia coli, Candida albicans and Bacillus subtilis black variant spores; It can inactivate poliovirus. The bactericidal rate reached 99.9999%, which is characterized by safety, reliability, no side effects, no irritation, completely killing COVID-19 and environmental protection.

STORAGE AND HANDLING

sealed storage in a cool, dry and dark place

WARNINGS

1. This product should be sealed and stored away from light;
2. Avoid prolonged exposure of liquids to air;
3. The product shall be stored in the environment within 4 ℃ - 40 ℃;
4. Valid for one year (use within 90 days after unsealing).